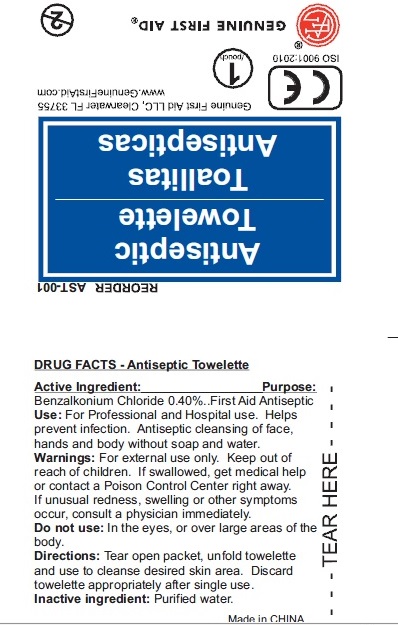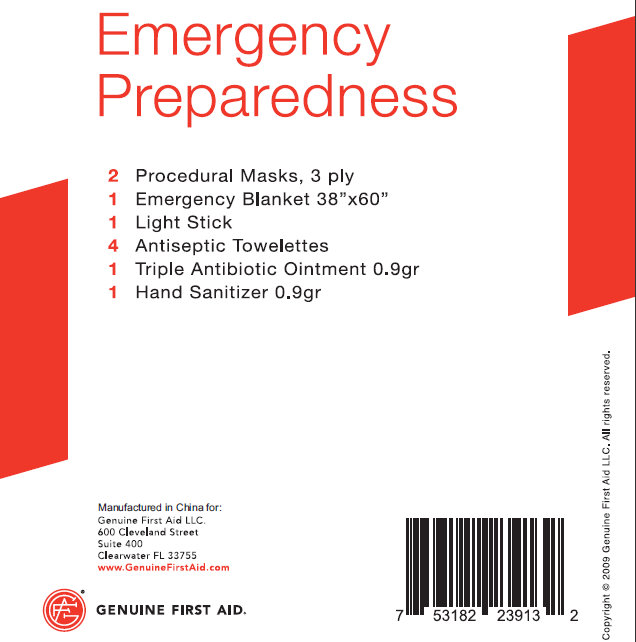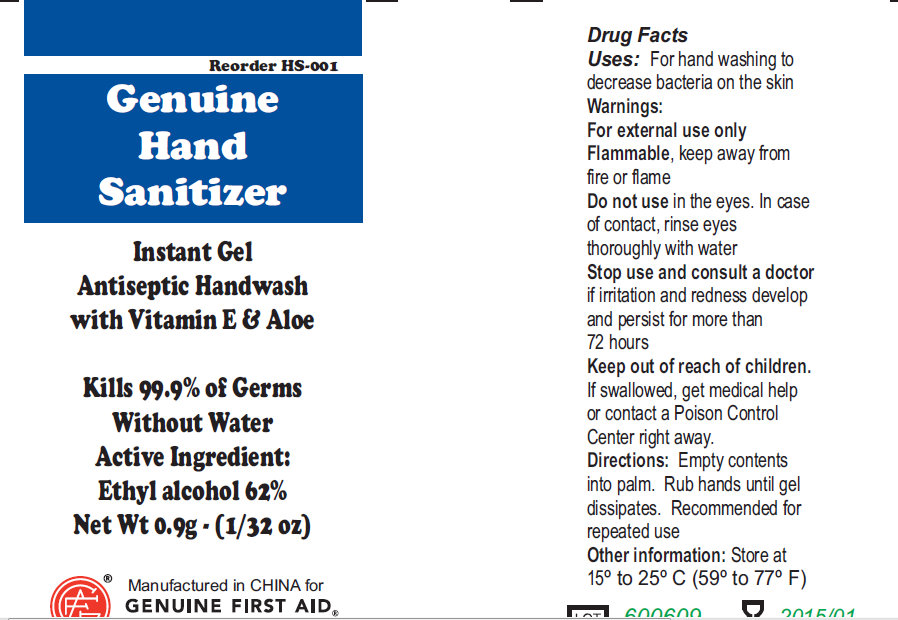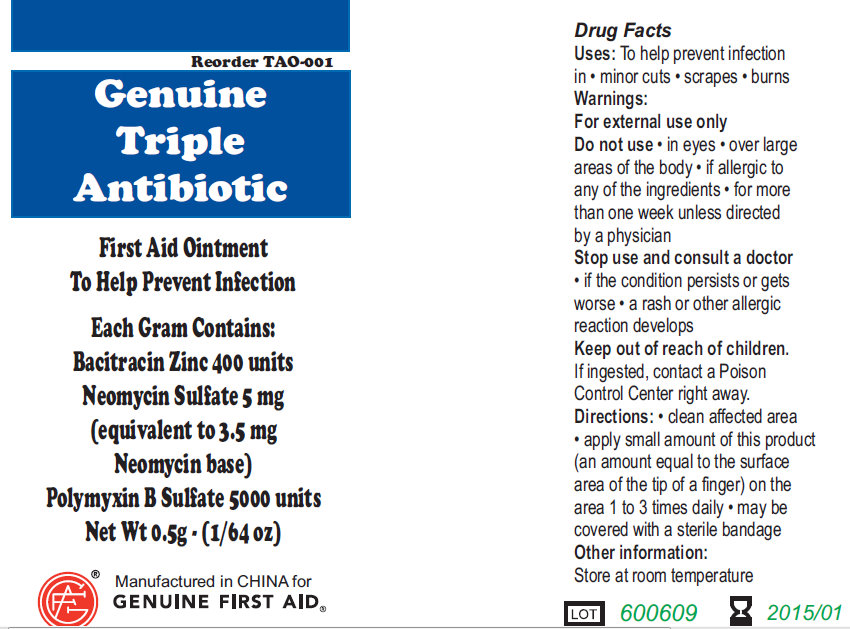 DRUG LABEL: Emergency Preparedness
NDC: 52124-0115 | Form: KIT | Route: TOPICAL
Manufacturer: Genuine First Aid LLC
Category: otc | Type: HUMAN OTC DRUG LABEL
Date: 20100602

ACTIVE INGREDIENTS: ALCOHOL 62 g/100 g; BENZALKONIUM CHLORIDE 0.40 mL/100 mL; BACITRACIN ZINC 400 [iU]/1 g; NEOMYCIN SULFATE 5 mg/1 g; POLYMYXIN B SULFATE 5000 [iU]/1 g
INACTIVE INGREDIENTS: WATER

Emergency Preparedness

Active Ingredient:
Ethyl Alcohol 62 %

PURPOSE

Uses: For hand washing to decrease bacteria on the skin

Warnings:
For external use only
Flammable, keep away from fire or flame

Do not use in the eyes. In case of contact, rinse eyes thoroughly with water.

Stop use and consult a doctor if irritation and redness develop and persist for more than 72 hours.

Keep out of reach of children.

If swallowed, get medical help or contact a Poison Control Center right away.

Directions:

Empty contents into palm. Rub hands until gel dissipates. Recommended for repeated use.

Other Information: Store at 15 to 25 degree Celsius (59 to 77 degree Fahrenheit)

PACKAGE LABEL

Genuine Hand Sanitizer
Instant Gel
Antiseptic Handwash
with Vitamin E and Aloe
Kills 99.9 percent of germs
Without Water
Net Wt 0.9g (1/32 oz)
Manufactured in China For
Genuine First Aid

Active Ingredient: Purpose

Benzalkonium Chloride 0.40%... First Aid Antiseptic

PURPOSE

Use: For Professional and Hospital use. Helps prevent infection. Antiseptic cleansing of face, hands and body without soap and water.

WARNINGS

Warning: For external use only.

Keep out of reach of children: If swallowed, get medical help or contact a Poison Control Center right away.

Stop use if unusual redness, swelling or other symptoms occur. Consult a physician immediately.

Do not use in the eyes or over large areas of the body.

WHEN USING

Directions: Tear open packet, unfold towelette and use to cleanse desired skin area. Discard
towelette appropriately after single use.

Inactive Ingredient: Purified water

DESCRIPTION

LOT/EXP: Made in CHINA
20130301

PACKAGE LABEL

Antiseptic Towelette
Genuine First Aid LLC, Clearwater FL 33755
www.GenuineFirstAid.com
GENUINE FIRST AID

Active Ingredient: .........Bacitracin Zinc 400 units
Neomycin Sulfate 5mg (equivalent to 3.5 mg Neomycin base)
Polymyxin B Sulfate 5000 units

PURPOSE

Uses: To help prevent infection
in * minor cuts * scrapes * burns

Warnings:
For external use only.

Do not use: in eyes; over large areas of the body; If allergic to any of the ingredients: for more
than one week unless directed by a physician.

Stop use and consult a doctor : if the condition persists or gets worse; a rash or other allergic
reaction develops

Keep out of reach of children.
If ingested, contact a Poison
Control Center right away.

WHEN USING

Directions: clean affected area; apply small amount of this product
(an amount equal to the surface area of the tip of a finger) on the
area 1 to 3 times daily * may be covered with a sterile bandage

Other information:
Store at room temperature.

PACKAGE LABEL

Genuine Triple Antibiotic
First Aid Ointment
To Help Prevent Infection
Each Gram Contains:
Bacitracin Zinc 400 units
Neomycin Sulfate 5 mg
(equivalent to 3.5 mg
Neomycin base)
Polymyxin B Sulfate 5000 units
Net Wt. 0.5g * (1/64 oz)
* Manufactured in CHINA for
GENUINE FIRST AID.

PACKAGE LABEL

Emergency Preparedness

2 Procedural Masks, 3 ply

1 Emergency Blanket 38" x 60"

1 Light Stick

4 Antiseptic Towelettes

1 Triple Antibiotic Ointment 0.9 gr

1 Hand Sanitizer 0.9 gr

Manufactured in China for:
Genuine First Aid LLC.
600 Cleveland Street
Suite 400
Clearwater FL 33755
www.GenuineFirstAid.com
GENUINE FIRST AID

Copyright 2009 Genuine First Aid LLC. All rights reserved.